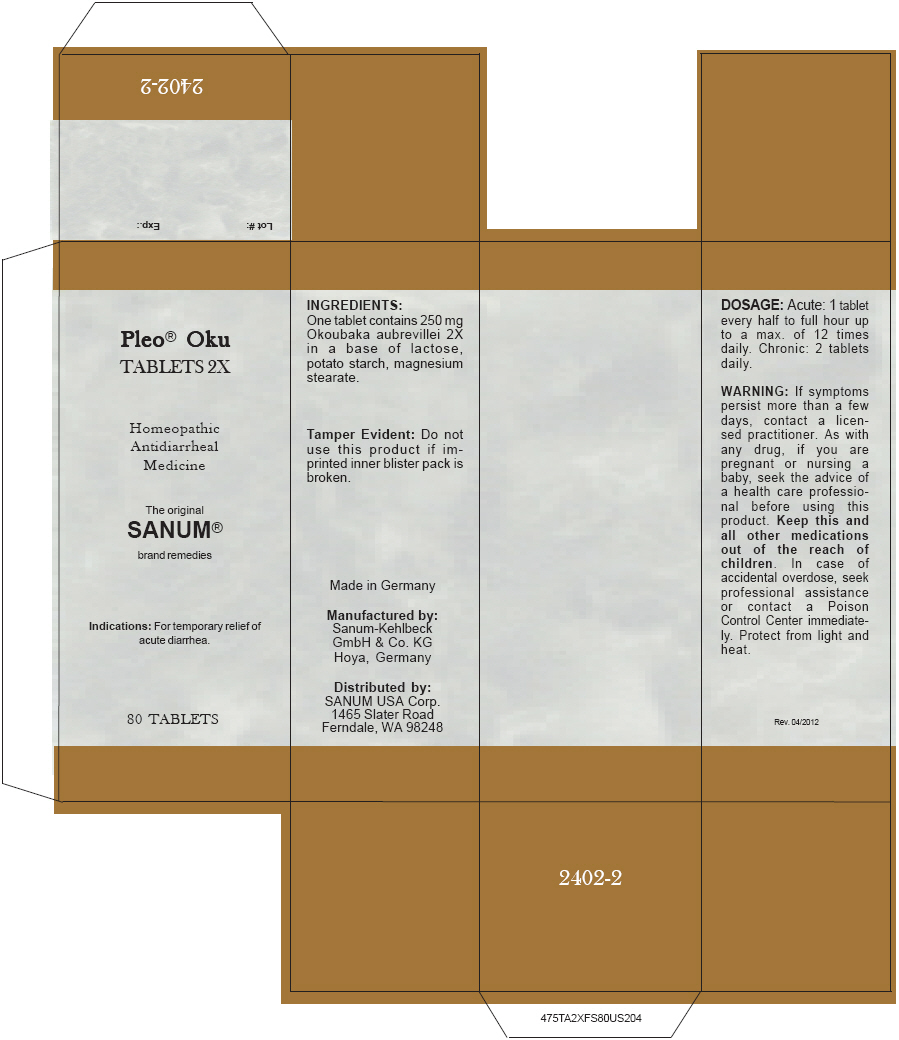 DRUG LABEL: Pleo Oku
NDC: 60681-2402 | Form: TABLET
Manufacturer: Sanum-Kehlbeck GmbH & Co. KG
Category: homeopathic | Type: HUMAN OTC DRUG LABEL
Date: 20120706

ACTIVE INGREDIENTS: OKOUBAKA AUBREVILLEI BARK 2 [hp_X]/1 1
INACTIVE INGREDIENTS: LACTOSE; STARCH, POTATO; MAGNESIUM STEARATE

Pleo® Oku TABLETS 2X

PURPOSE

Homeopathic Antidiarrheal Medicine

Indications

For temporary relief of acute diarrhea.

ACTIVE INGREDIENT

INGREDIENTS

One tablet contains 250 mg Okoubaka aubrevillei 2X in a base of lactose, potato starch, magnesium stearate.

Tamper Evident

Do not use this product if imprinted inner blister pack is broken.

DOSAGE

Acute

1 tablet every half to full hour up to a max. of 12 times daily.

Chronic

2 tablets daily.

WARNING

lf symptoms persist more than a few days, contact a licensed practitioner. As with any drug, if you are pregnant or nursing a baby, seek the advice of a health care professional before using this product.

KEEP OUT OF REACH OF CHILDREN

Keep this and all other medications out of the reach of children. In case of accidental overdose, seek professional assistance or contact a Poison Control Center immediately.

STORAGE AND HANDLING

Protect from light and heat.

Rev. 04/2012

Manufactured by:
Sanum-Kehlbeck
GmbH & Co. KG
Hoya, Germany

Distributed by:
SANUM USA Corp.
1465 Slater Road
Ferndale, WA 98248

PRINCIPAL DISPLAY PANEL - 80 Tablet Carton

Pleo® Oku
TABLETS 2X

Homeopathic
Antidiarrheal
Medicine

The original
SANUM®

brand remedies

Indications: For temporary relief of
acute diarrhea.

80 TABLETS